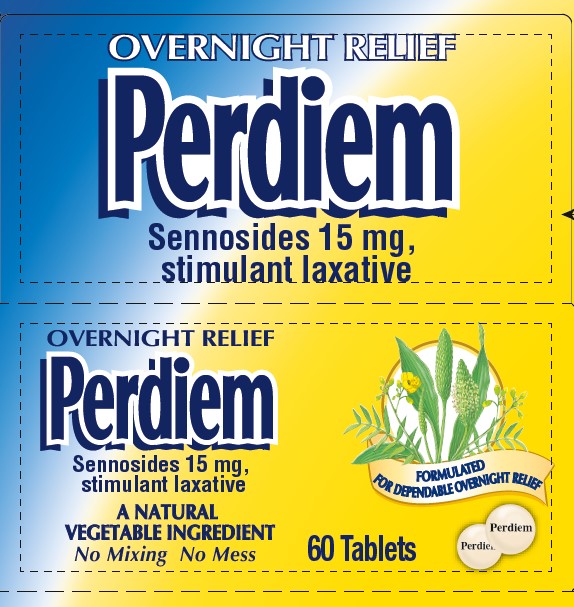 DRUG LABEL: Perdiem
NDC: 0067-8143 | Form: TABLET
Manufacturer: Haleon US Holdings LLC
Category: otc | Type: HUMAN OTC DRUG LABEL
Date: 20250116

ACTIVE INGREDIENTS: SENNOSIDES 15 mg/1 1
INACTIVE INGREDIENTS: ACACIA; CALCIUM CARBONATE; CARNAUBA WAX; DIBASIC CALCIUM PHOSPHATE DIHYDRATE; MAGNESIUM STEARATE; METHYLPARABEN; MICROCRYSTALLINE CELLULOSE; POLYETHYLENE GLYCOL 3350; POLYVINYL ALCOHOL, UNSPECIFIED; POVIDONE, UNSPECIFIED; STARCH, CORN; PROPYLPARABEN; SILICON DIOXIDE; SODIUM BENZOATE; SODIUM LAURYL SULFATE; SUCROSE; FERROUS OXIDE; TALC; TITANIUM DIOXIDE

Drug Facts

Active Ingredient

Sennosides 15 mg

Purpose

Stimulant laxative

Uses

- relieves occasional constipation (irregularity)
- generally produces bowel movement in 6 to 12 hours

Warnings

Do Not Use

- laxative products when abdominal pain, nausea or vomiting are present unless directed by a doctor
- for a period longer than 1 week unless directed by a doctor

Ask Doctor before use if you have

noticed a sudden change in bowel habits that persists over a period of 2 weeks

Ask a doctor or pharmacist before use if you

are taking any other drug. Laxatives may affect how other drugs work. Take this product 2 or more hours before or after other drugs.

Stop use and ask a doctor if

rectal bleeding or failure to have a bowel movement occur after use of a laxative. These may be signs of a serious condition.

Directions

- take preferably before bedtime or as directed by a doctor.
- swallow tablet(s) with a glass of water
- swallow tablets whole, do not crush, break or chew

Adults and children 12 years of age and older | 2 tablets once or twice daily
Children 6 to under 12 years of age | 1 tablet once or twice daily
Children under 6 years of age | ask a doctor

Other information

● each tablet contains:calcium 40 mg

● store at 20°C-25°C (68°F-77°F).

Inactive ingredients

acacia, calcium carbonate, carnauba wax, dibasic calcium phosphate dihydrate, magnesium stearate, methylparaben, microcrystalline cellulose, pharmaceutical ink, polyethylene glycol, polyvinyl alcohol, povidone, pregelatinized starch, propylparaben, silicon dioxide, sodium benzoate, sodium lauryl sulfate, sucrose, synthetic iron oxides, talc, titanium dioxide

Questions or comments?

call 1-800-452-0051

Package/Label Principal Display Panel

OVERNIGHT RELIEF

Perdiem

Sennosides 15 mg,

Stimulant laxative

A NATURAL VEGETABLE INGREDIENT

NO MIXING NO MESS

FORMULATED FOR DEPENDABLE OVERNIGHT RELIEF

60 Tablets

Do not use if printed inner safety seal under cap is broken or missing.